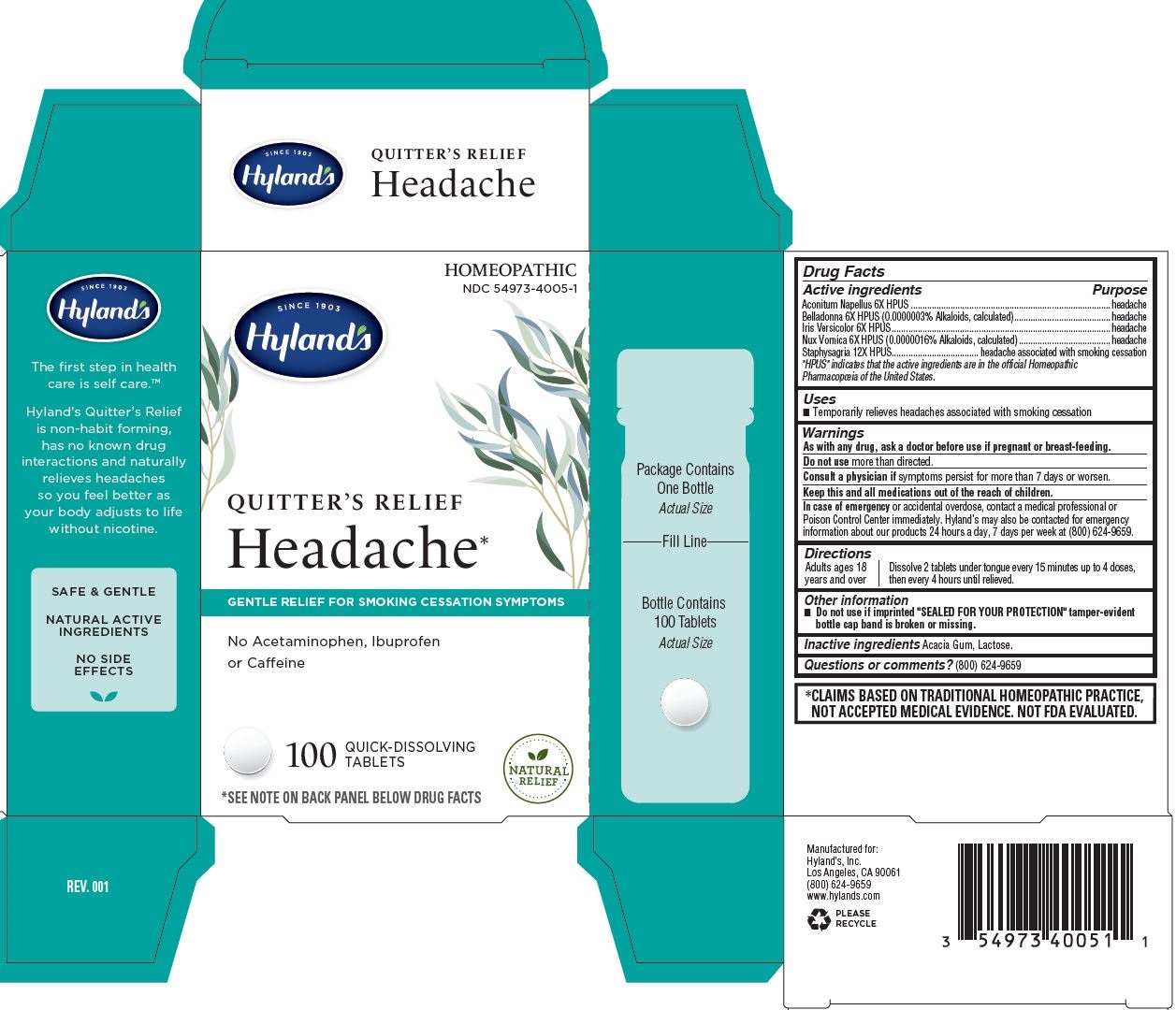 DRUG LABEL: Quitters Relief Headache
NDC: 54973-4005 | Form: TABLET
Manufacturer: Hyland's Inc.
Category: homeopathic | Type: HUMAN OTC DRUG LABEL
Date: 20221213

ACTIVE INGREDIENTS: IRIS VERSICOLOR ROOT 6 [hp_X]/1 1; DELPHINIUM STAPHISAGRIA SEED 12 [hp_X]/1 1; STRYCHNOS NUX-VOMICA SEED 6 [hp_X]/1 1; ACONITUM NAPELLUS 6 [hp_X]/1 1; ATROPA BELLADONNA 6 [hp_X]/1 1
INACTIVE INGREDIENTS: LACTOSE MONOHYDRATE; ACACIA

Hyland's Quitter's Relief Headache

PURPOSE

Temporarily relieves headaches associated with smoking cessation

Drug Facts

Active ingredients

Active ingredients | Purpose
Aconitum Napellus 6X HPUS | headache
Belladonna 6X HPUS (0.0000003% Alkaloids, calculated) | headache
Iris Versicolor 6X HPUS | headache
Nux Vomica 6X HPUS (0.0000016% Alkaloids, calculated) | headache
Staphysagria 12X HPUS | headache

"HPUS" indicates that the active ingredients are in the official Homeopathic

Pharmacopoeia of the United States.

Uses

■ Temporarily relieves headaches associated with smoking cessation

Warnings

PREGNANCY OR BREAST FEEDING

As with any drug, ask a doctor before use if pregnant or breast-feeding.

Do not use more than directed.

ASK DOCTOR

Consult a physician if symptoms persist for more than 7 days or worsen.

KEEP OUT OF REACH OF CHILDREN

Keep this and all medications out of the reach of children.

OVERDOSAGE

In case of emergency or accidental overdose, contact a medical professional or Poison Control Center immediately. Hyland’s may also be contacted for emergency information about our products 24 hours a day, 7 days per week at (800) 624-9659.

Directions

Adults ages 18

years and over

Dissolve 2 tablets under tongue every 15 minutes up to 4 doses,

then every 4 hours until relieved.

Other information

■ Do not use if imprinted "SEALED FOR YOUR PROTECTION" tamper-evident bottle cap band is broken or missing.

Inactive ingredients

Acacia Gum, Lactose.

Questions or comments?

(800) 624-9659

*CLAIMS BASED ON TRADITIONAL HOMEOPATHIC PRACTICE, NOT ACCEPTED MEDICAL EVIDENCE. NOT FDA EVALUATED.

PACKAGE LABEL - PRINCIPAL DISPLAY PANEL

HOMEOPATHIC

NDC 54973-4005-1

SINCE 1903

Hyland's

QUITTER’S RELIEF

Headache*

GENTLE RELIEF FOR SMOKING CESSATION SYMPTOMS

No Acetaminophen, Ibuprofen

or Caffeine

100 QUICK-DISSOLVING

TABLETS

NATURAL

RELIEF

*SEE NOTE ON BACK PANEL BELOW DRUG FACTS